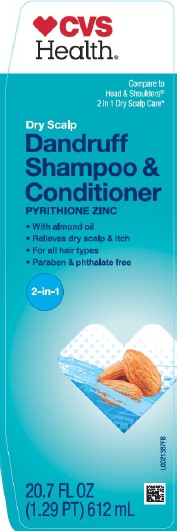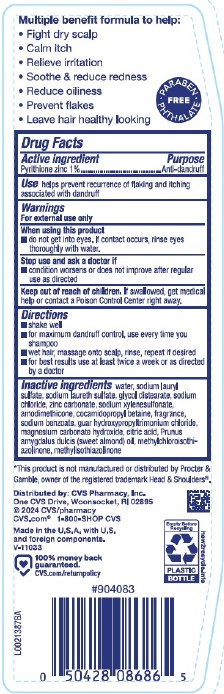 DRUG LABEL: Dry Scalp Care
NDC: 59779-296 | Form: SHAMPOO
Manufacturer: CVS Pharmacy, Inc.
Category: otc | Type: HUMAN OTC DRUG LABEL
Date: 20260202

ACTIVE INGREDIENTS: PYRITHIONE ZINC 10 mg/1 mL
INACTIVE INGREDIENTS: WATER; SODIUM LAURYL SULFATE; SODIUM LAURETH SULFATE; GLYCOL DISTEARATE; SODIUM CHLORIDE; ZINC CARBONATE; SODIUM XYLENESULFONATE; AMODIMETHICONE (800 CST); COCAMIDOPROPYL BETAINE; SODIUM BENZOATE; GUAR HYDROXYPROPYLTRIMONIUM CHLORIDE (1.7 SUBSTITUENTS PER SACCHARIDE); MAGNESIUM CARBONATE HYDROXIDE; CITRIC ACID MONOHYDRATE; ALMOND OIL; METHYLCHLOROISOTHIAZOLINONE; METHYLISOTHIAZOLINONE

CVS 296.007/296AT, AV, AW
Dandruff Shampoo, Dry Scalp 2 in 1

claims

Multiple benefit formula to help:

- Fight dry scalp
- Calm itch
- Relieve irritation
- Soothe & reduce redness
- Reduce oiliness
- Prevent flakes
- Leave hair healthy looking

PARABEN-PHTHALATE FREE

Active ingredient

Pyrithione zinc 1%

Purpose

Anti-dandruff

Use

helps prevent recurrence flaking and itching associated with dandruff

Warnings

For external use only

When using this product

- do not get into eyes. if contact occurs, rinse eyes thoroughly with water.

Stop use and ask a doctor if

- condition worsens or does not improve after regular use as directed

Keep out of reach of children.

If swallowed, get medical help or contact a Poison Control Center right away.

Directions

- shake well
- for maximum dandruff control, use every time you shampoo
- wet hair, massage onto scalp, rinse, repeat if desired
- for best results use at least twice a week or as directed by a doctor

Inactive ingredients

water, sodium lauryl sulfate, sodium laureth sulfate, glycol distearate, sodium chloride, zinc carbonate, sodium xylenesulfonate, amodimethicone, cocamidopropyl betaine, fragrance, sodium benzoate, guar hydroxypropyltrimonium chloride, magnesium carbonate hydroxide, citric acid, Prunus amygdalus dulcis (sweet almond) oil, methylchloroisothiazolinone, methylisothiazolinone

Disclaimer

*This product is not manufactured or distributed by Procter & Gamble, owner of the registered trademark Head & Shoulders®.

Adverse reactions

Distributed by: CVS Pharmacy, Inc.

One CVS Drive, Woonsocket, RI 02895

©2024 CVS/Pharmacy

CVS.com 1-800-SHOP CVS

Made in the U.S.A. of U.S. and foreign components.

100% money back guaranteed

CVS.com/returnpolicy

Empty Before Recycling

PLASTIC BOTTLE

how2recycle.info

Principal display panel

CVS Health®

Compare to Head & Shoulders® 2 in 1 Dry Scalp Care*

Dry Scalp

Dandruff Shampoo & Conditioner

PYRITHIONE ZINC

- With almond oil
- Relieves dry scalp & itch
- For all hair types
- Paraben & phthalate free

2-in-1

20.7 FL OZ (1.29 PT) 612 mL